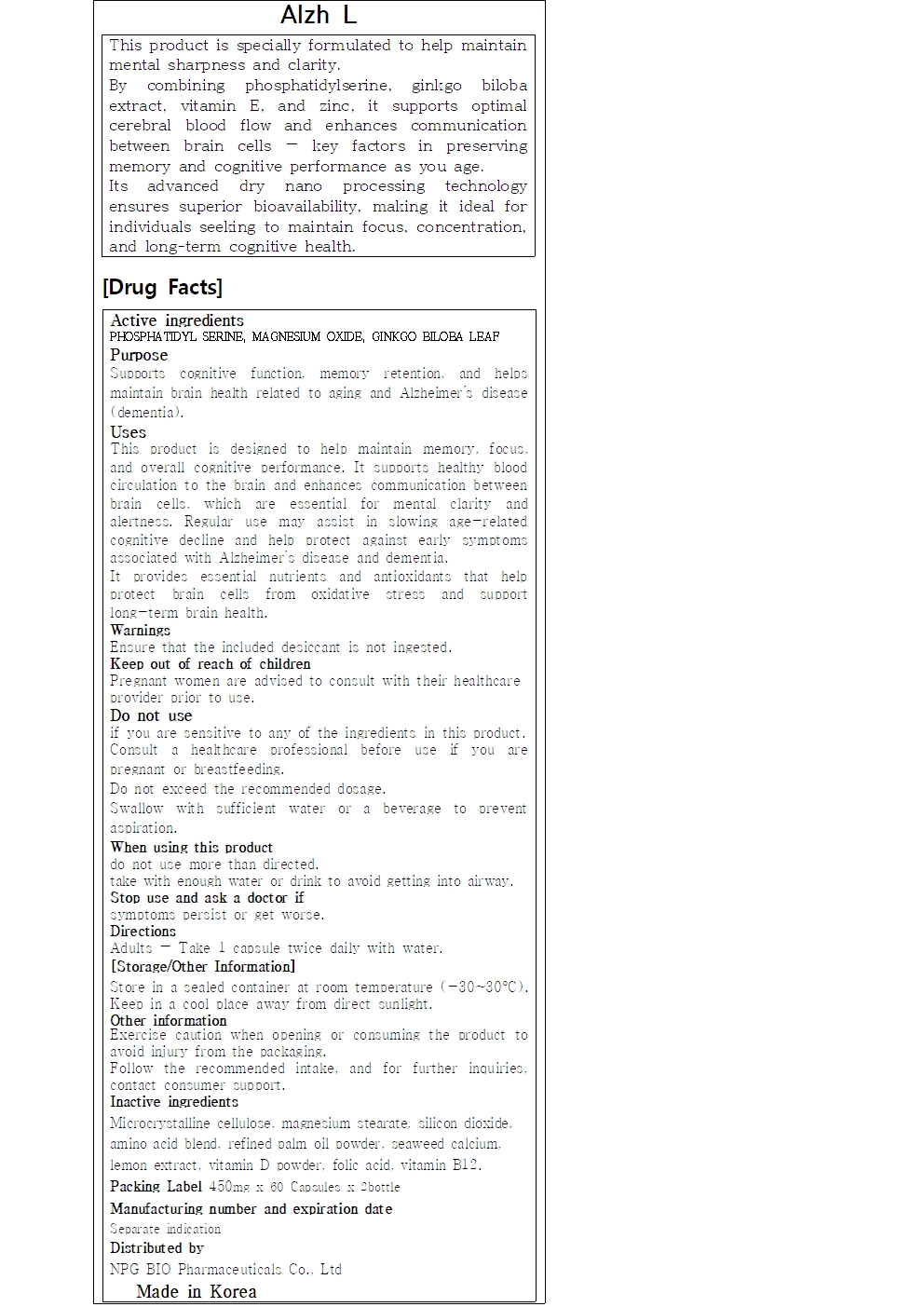 DRUG LABEL: Alzh L
NDC: 84540-230 | Form: TABLET
Manufacturer: NPG Bio Pharmaceuticals Co.,Ltd.
Category: otc | Type: HUMAN OTC DRUG LABEL
Date: 20251218

ACTIVE INGREDIENTS: PHOSPHATIDYL SERINE 214.43 mg/450 mg; GINKGO BILOBA LEAF 75.02 mg/450 mg; MAGNESIUM OXIDE 11.27 mg/450 mg
INACTIVE INGREDIENTS: LEUCINE; SILICON DIOXIDE; GLUCOSAMINE HYDROCHLORIDE; CORDYCEPS MILITARIS FRUITING BODY; HYDROXYPROPYL METHYLCELLULOSE; MICROCRYSTALLINE CELLULOSE; FISH OIL; CHOLECALCIFEROL; FOLIC ACID; CALCIUM; ZINC OXIDE; AMINO ACIDS, SOURCE UNSPECIFIED; CYANOCOBALAMIN; MAGNESIUM STEARATE

84540-230 Alzh L TABLET

Active Ingredients

PHOSPHATIDYL SERINE, MAGNESIUM OXIDE, GINKGO BILOBA LEAFPHOSPHATIDYL SERINE, MAGNESIUM OXIDE, GINKGO BILOBA LEAF

Purposes

Supports cognitive function, memory retention, and helps maintain brain health related to aging and Alzheimer’s disease (dementia).

Uses

This product is designed to help maintain memory, focus, and overall cognitive performance. It supports healthy blood circulation to the brain and enhances communication between brain cells, which are essential for mental clarity and alertness. Regular use may assist in slowing age-related cognitive decline and help protect against early symptoms associated with Alzheimer’s disease and dementia.

It provides essential nutrients and antioxidants that help protect brain cells from oxidative stress and support long-term brain health.

Warnings

Do not use if you are sensitive to any of the ingredients in this product. Consult a healthcare professional before use if you are pregnant or breastfeeding.
Do not exceed the recommended dosage.
Swallow with sufficient water or a beverage to prevent aspiration.

Warnings

Keep out of reach of children
Pregnant women are advised to consult with their healthcare provider prior to use.

Warnings

Stop use and ask a doctor if symptoms persist or get worse.

Warnings

When using this product do not use more than directed.

take with enough water or drink to avoid getting into airway.

Warnings

Ensure that the included desiccant is not ingested.

Directions

Take 2 Capsuel daily, 1 capsule per serving, with water.

Inactive Ingredients

Microcrystalline cellulose, magnesium stearate, silicon dioxide, amino acid blend, refined palm oil powder, seaweed calcium, lemon extract, vitamin D powder, folic acid, vitamin B12.